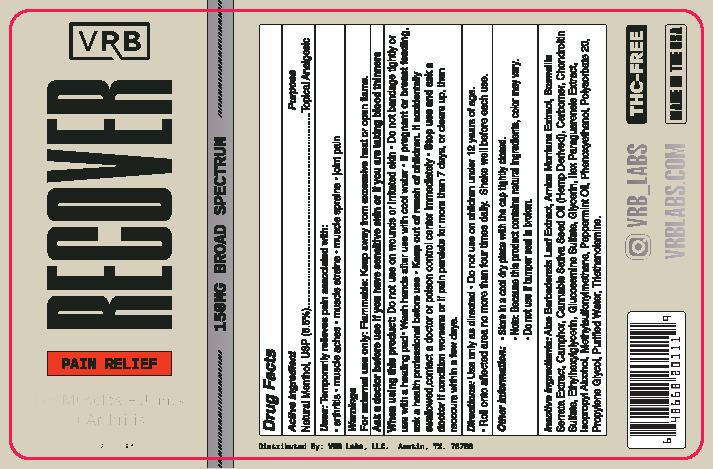 DRUG LABEL: Recover CBD Pro
NDC: 78308-007 | Form: GEL
Manufacturer: VRB Labs, LLC
Category: otc | Type: HUMAN OTC DRUG LABEL
Date: 20240108

ACTIVE INGREDIENTS: MENTHOL, UNSPECIFIED FORM 85 mg/1 mL
INACTIVE INGREDIENTS: ETHYLHEXYLGLYCERIN; ISOPROPYL ALCOHOL; PEPPERMINT OIL; PROPYLENE GLYCOL; TROLAMINE; WATER; ALOE VERA LEAF; POLYSORBATE 20; CARBOMER INTERPOLYMER TYPE A (ALLYL SUCROSE CROSSLINKED); ARNICA MONTANA; INDIAN FRANKINCENSE; CAMPHOR (SYNTHETIC); DIMETHYL SULFONE; GLUCOSAMINE SULFATE; CANNABIS SATIVA SEED OIL; CHONDROITIN SULFATE (SHARK); GLYCERIN; ILEX PARAGUARIENSIS LEAF; PHENOXYETHANOL

Recover Pro
V3 updated label

ACTIVE INGREDIENT

Natural Menthol, USP (8.5%)

PURPOSE

Topical Analgesic

INDICATIONS AND USAGE

Temporarily relieves pain associated with:

arthritis
muscle aches
muscle strains
muscle sprains
joint pain

WARNINGS

For external use only: Flammable: Keep away from excessive heat or open flame.

Ask a doctor before use is you have sensitive skin or if you are taking any blood thinners,

When using this product

Do not use on wounds or irritated skin

Do not bandage tightly or use with a heating pad

Wash hands after use with cool water

If pregnant or breast feeding, ask a health professional before use

Keep out of reach of children. If accidentally swallowed,contact a doctor or poison control center immediately

Stop use and ask a doctor if condition worsens or if pain persists for more than 7 days, or clears up, then reoccurs within a few days.

Keep out of reach of children. If accidentally swallowed, contact a doctor or poison control center immediately

DOSAGE AND ADMINISTRATION

Use only as directed

Do not use on children under 12 years of age.
Roll onto affected area no more than four times daily.

Shake well before each use.

INACTIVE INGREDIENT

Aloe Barbadensis Leaf Extract, Arnica Montana Extract, Boswellia Serrata Extract, Camphor, Cannabis Sativa Seed Oil (Hemp Derived), Carbomer, Chondroitin Sulfate, Ethylhexylglycerin, Glucosamine Sulfate, Glycerin, Ilex Paraguarensis Extract, Isopropyl Alcohol, Methylsulfonylmethane, Peppermint Oil, Phenoxyethanol, Polysorbate 20, Propylene Glycol, Purified Water,Triethanolamine.